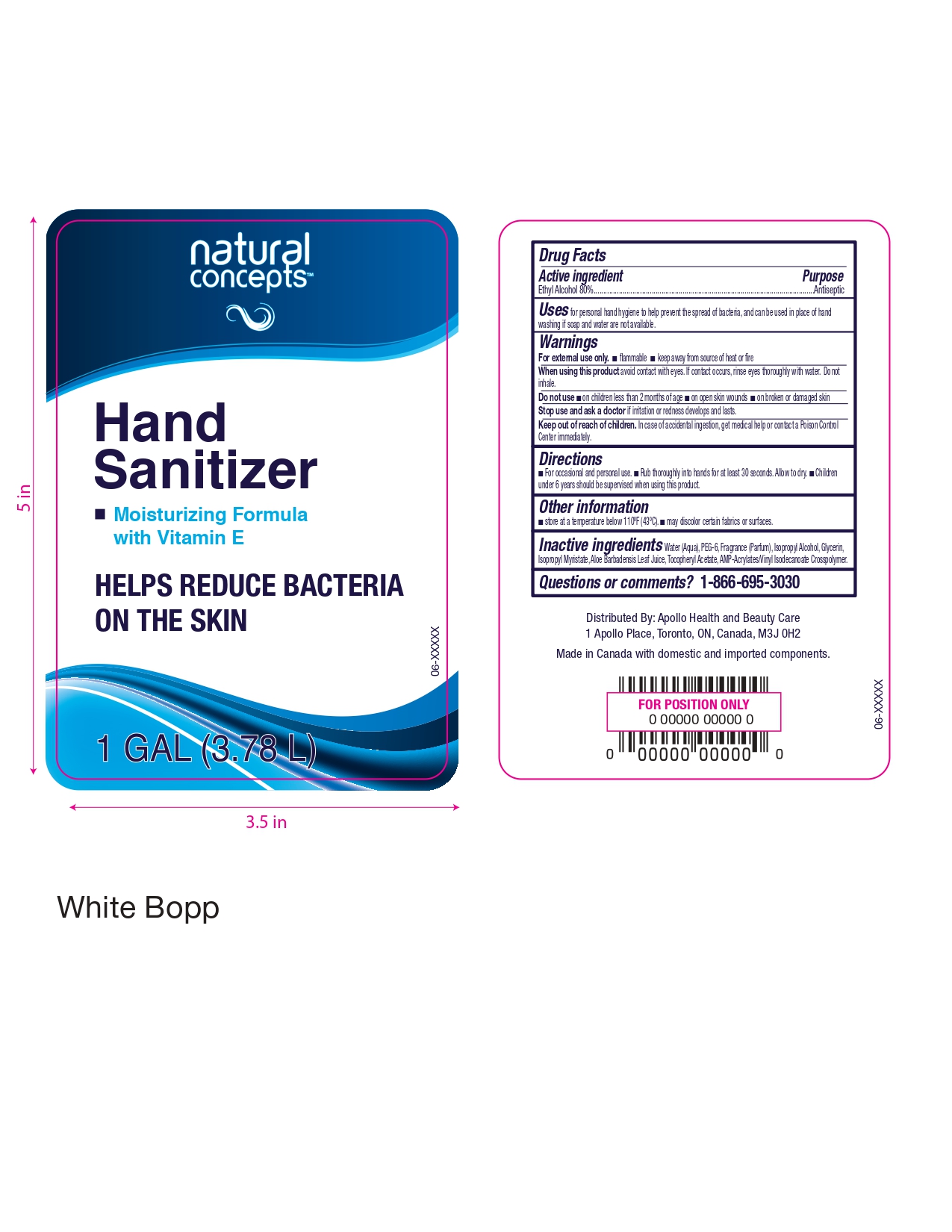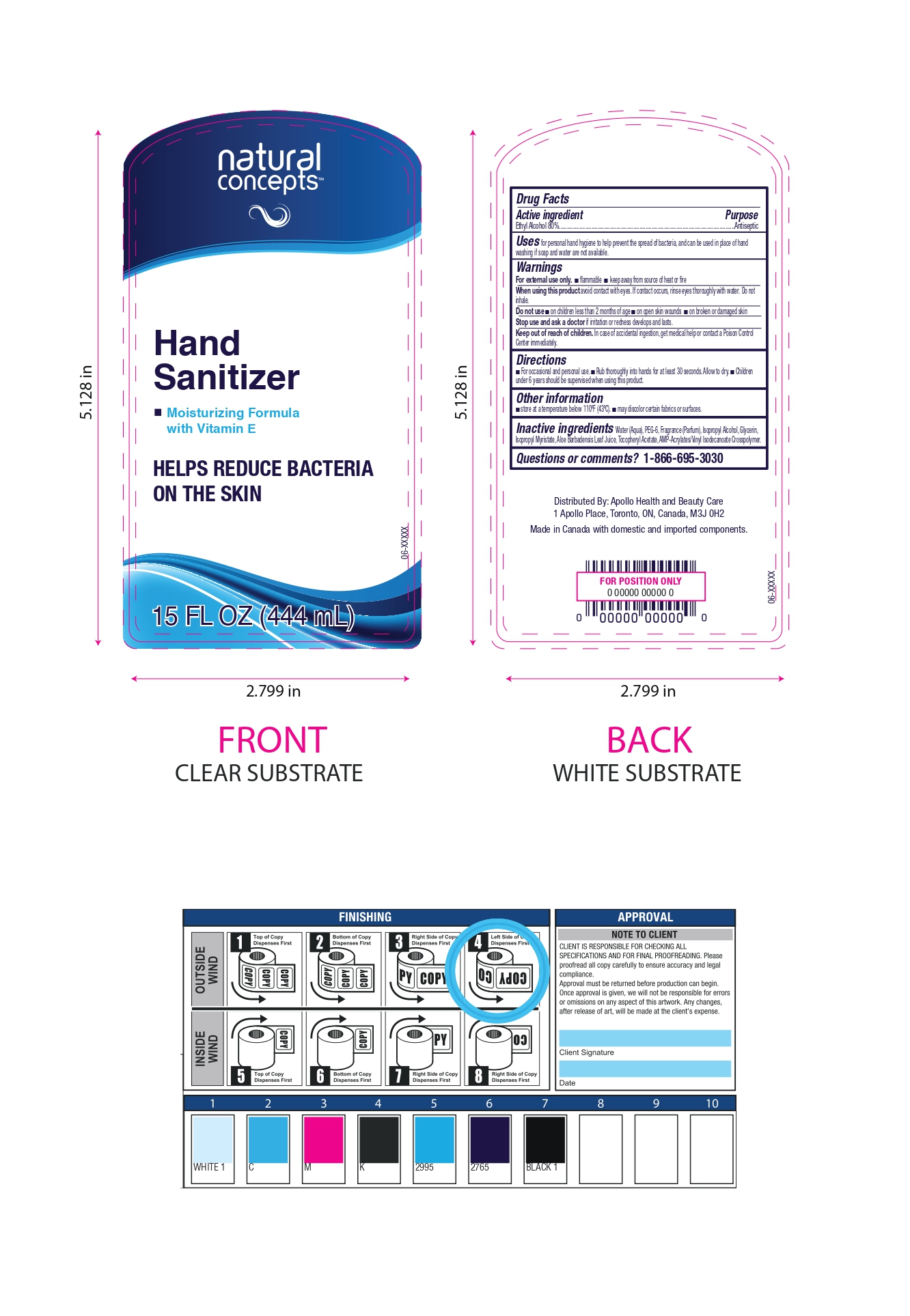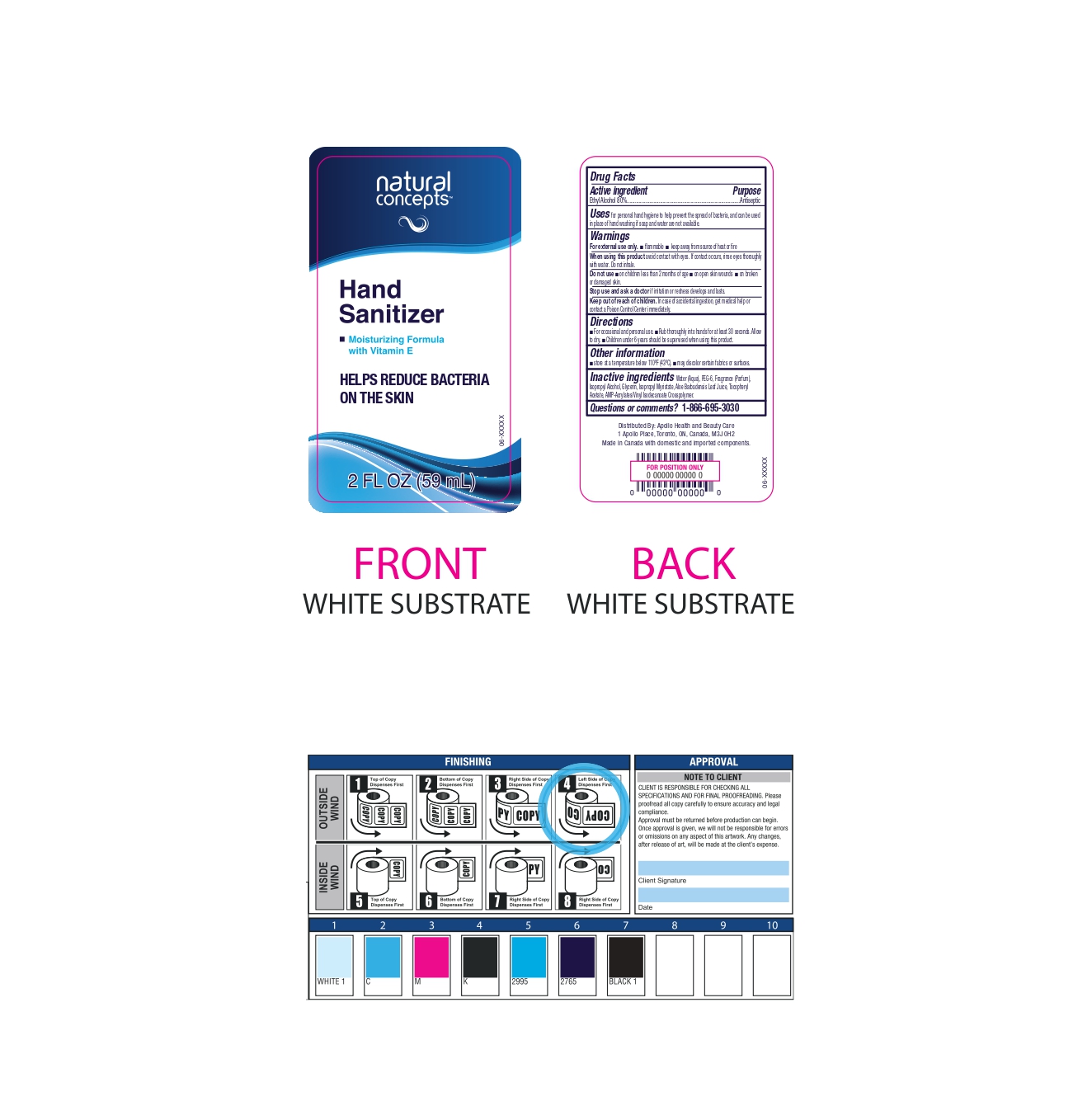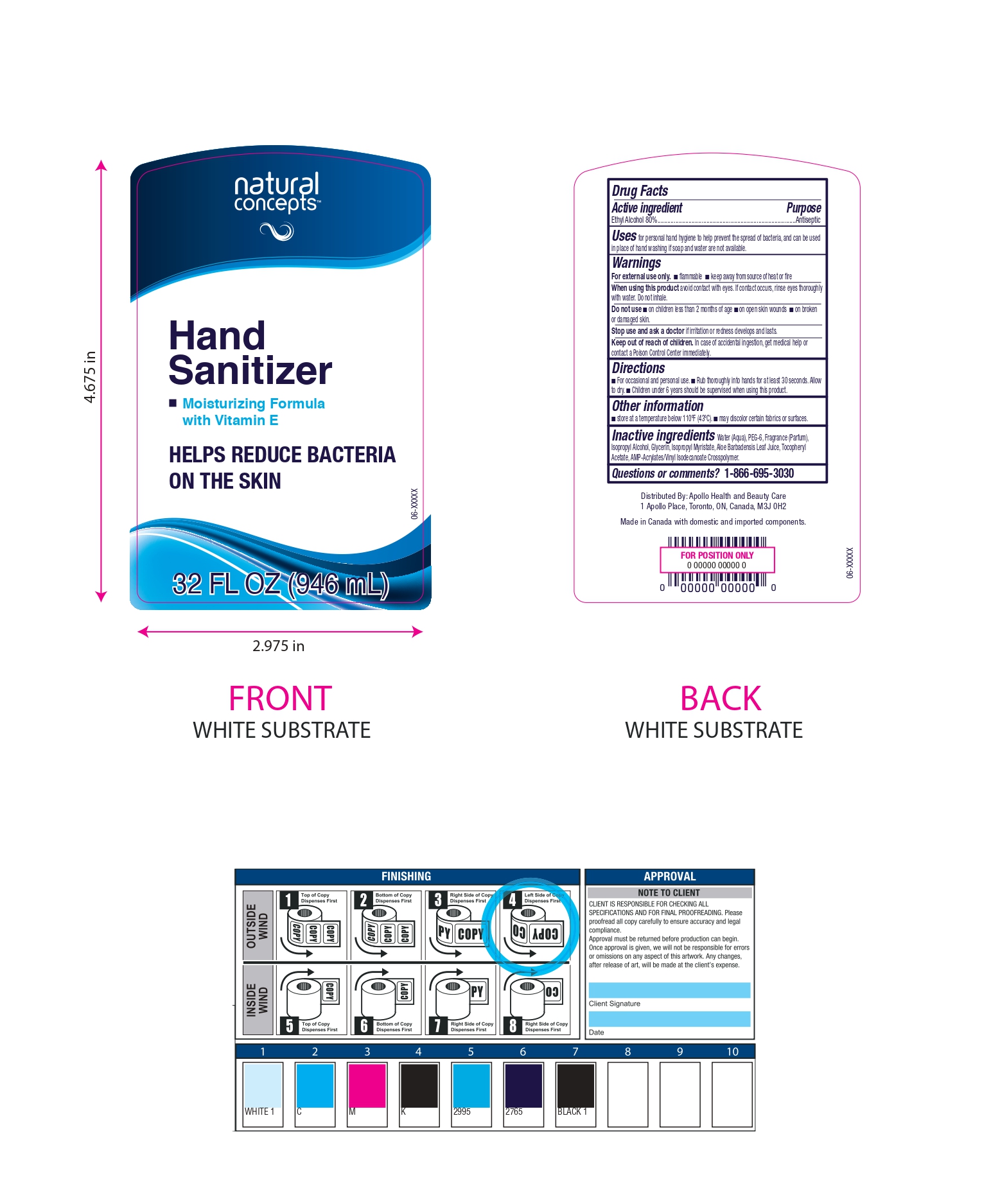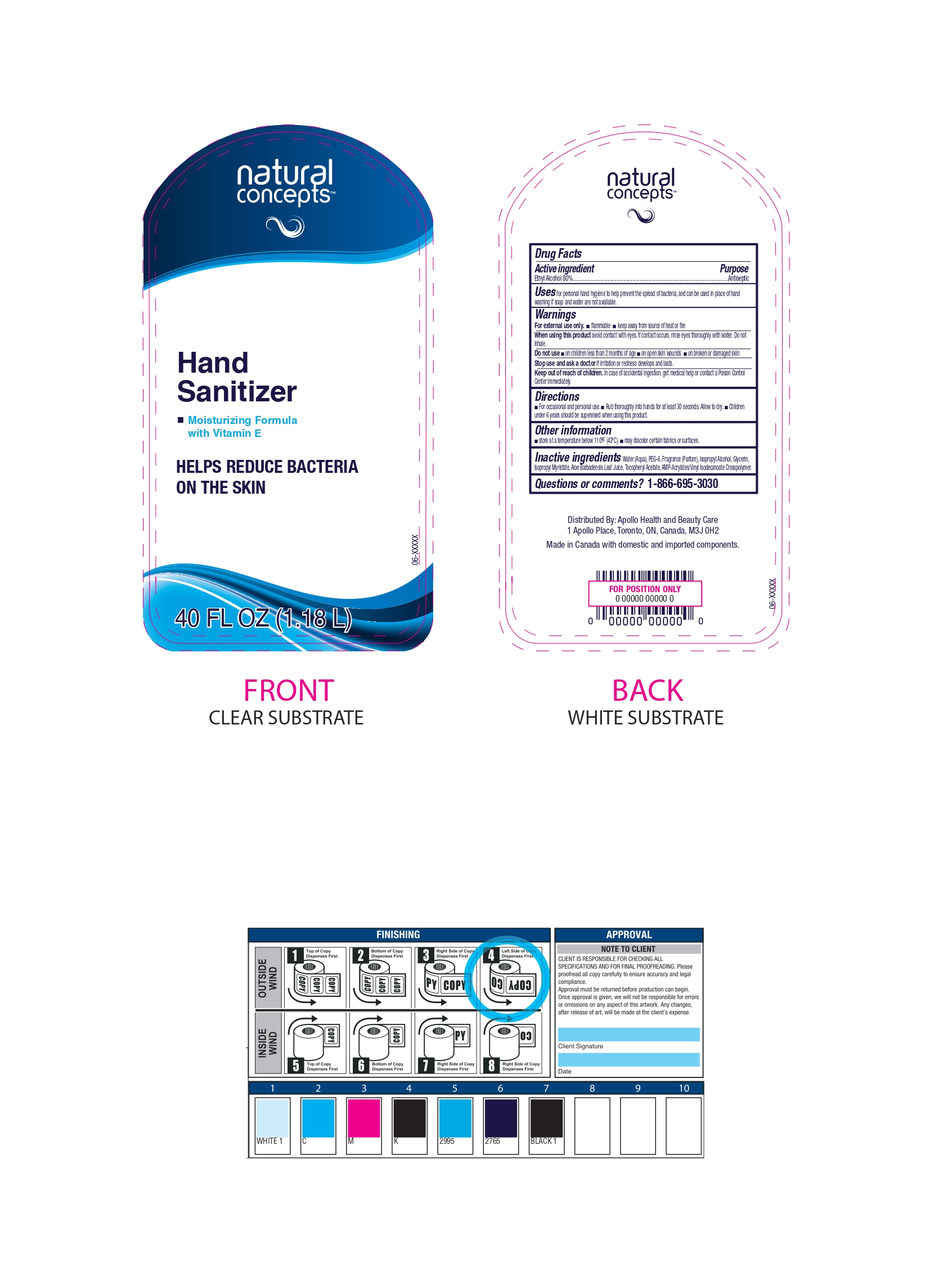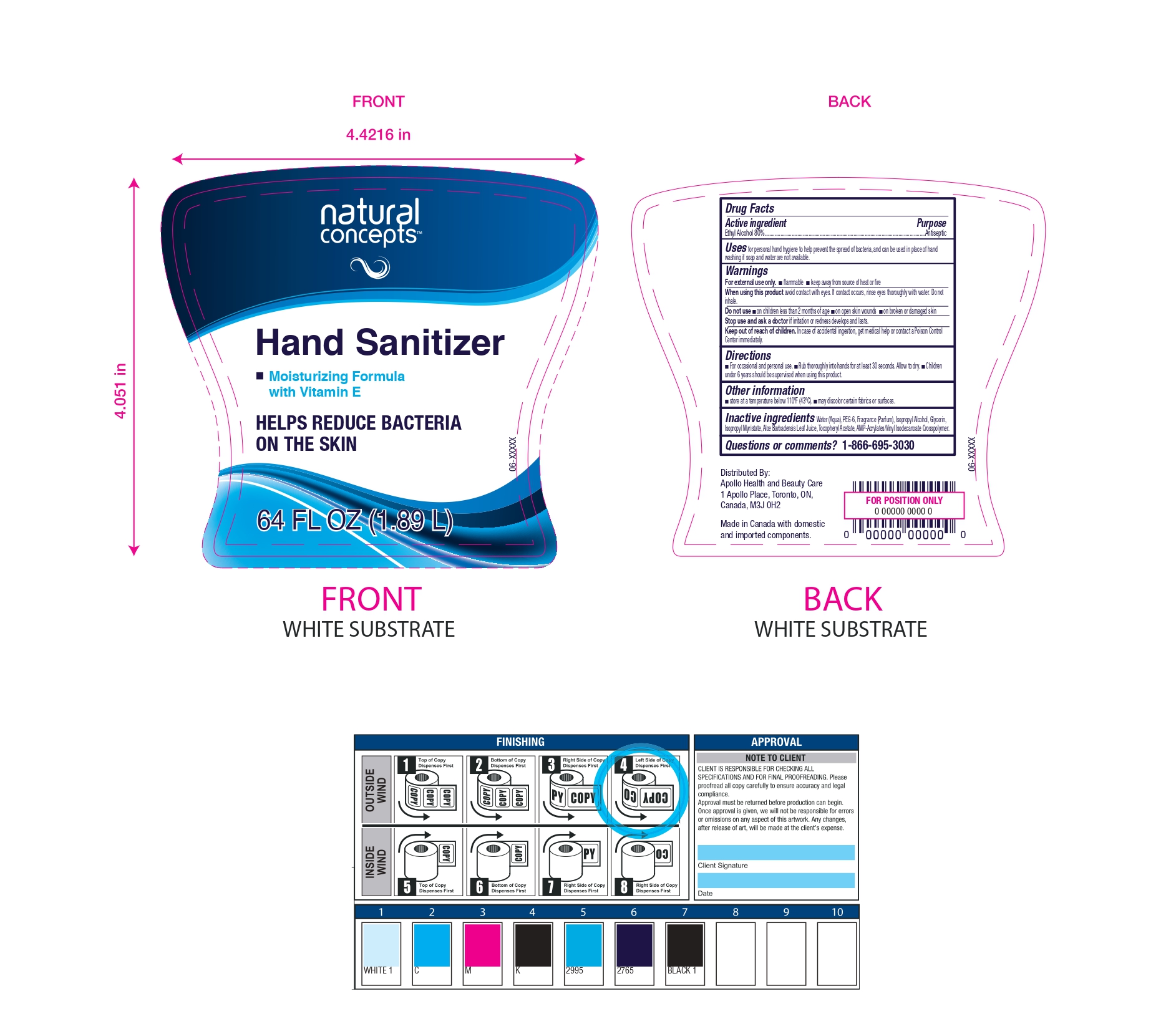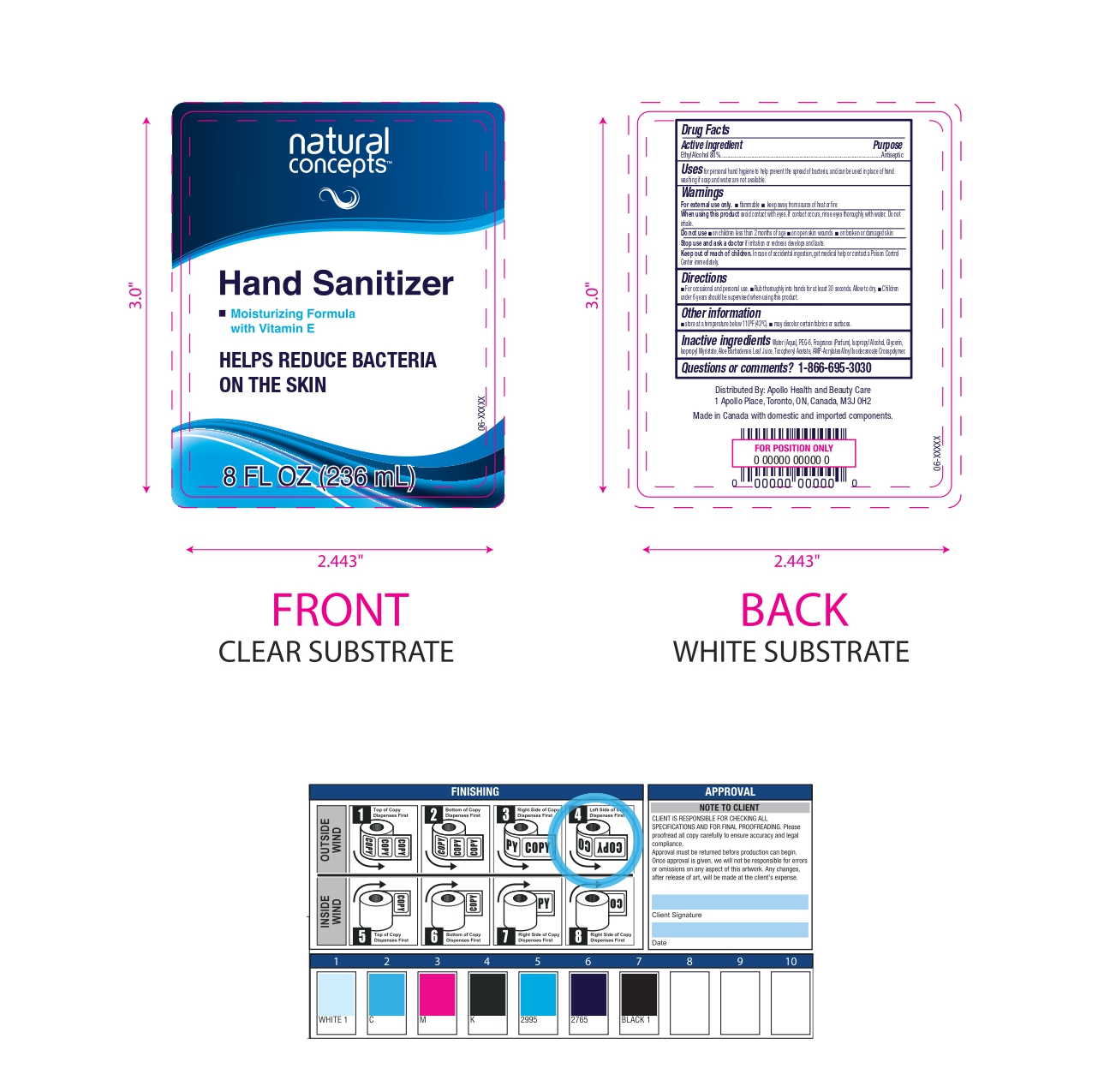 DRUG LABEL: Natural Concepts
NDC: 63148-526 | Form: GEL
Manufacturer: Apollo Health and Beauty Care Inc
Category: otc | Type: HUMAN OTC DRUG LABEL
Date: 20250105

ACTIVE INGREDIENTS: ALCOHOL 800 mg/1 mL
INACTIVE INGREDIENTS: WATER; POLYETHYLENE GLYCOL 300; ISOPROPYL ALCOHOL; GLYCERIN; ISOPROPYL MYRISTATE; ALOE VERA LEAF; .ALPHA.-TOCOPHEROL ACETATE, DL-; ACRYLATES/VINYL ISODECANOATE CROSSPOLYMER (10000 MPA.S NEUTRALIZED AT 0.5%)

NDC- 63148-526

Active Ingredients

Ethyl Alcohol (80%)

Purpose

Antiseptic

Uses

For Personal hand hygiene to help the spread of bacteria and can be used in place of hand washing if soap and water are not available.

Warnings

- For External use only
- Flammable
- Keep away from source of heat or fire.

When using this product

Avoid contact with eyes. If contact occurs, rinse thoroughly with water. Do not Inhale.

Do not use

- on children less than 2 months of age
- on open skin wounds
- on broken or damaged skin

Stop use and ask a doctor

If Irritation or redness develops and lasts.

Keep out of reach of children

In case of accidental ingestion, get medical help or contact a Poison Control Centre immediately

Directions

- For occasional and personal use
- Rub thoroughly into hands for at least 30 seconds. Allow to dry
- Children under 6 years should be supervised when using this product

Other Information

- Store at a temperature below 110^0F (43^0C)
- May discolor certain fabrics or surfaces

Inactive Ingredients

Water (Aqua), PEG-6, Fragrance (Parfum), Isopropyl Alcohol, Glycerin, Isopropyl Myristate, Aloe Barbadensis Leaf Juice, Tocopheryl Acetate, AMP-Acrylates/Vinyl Isodecanate Crosspolymer

Questions or comments ?

1-866-695-3030